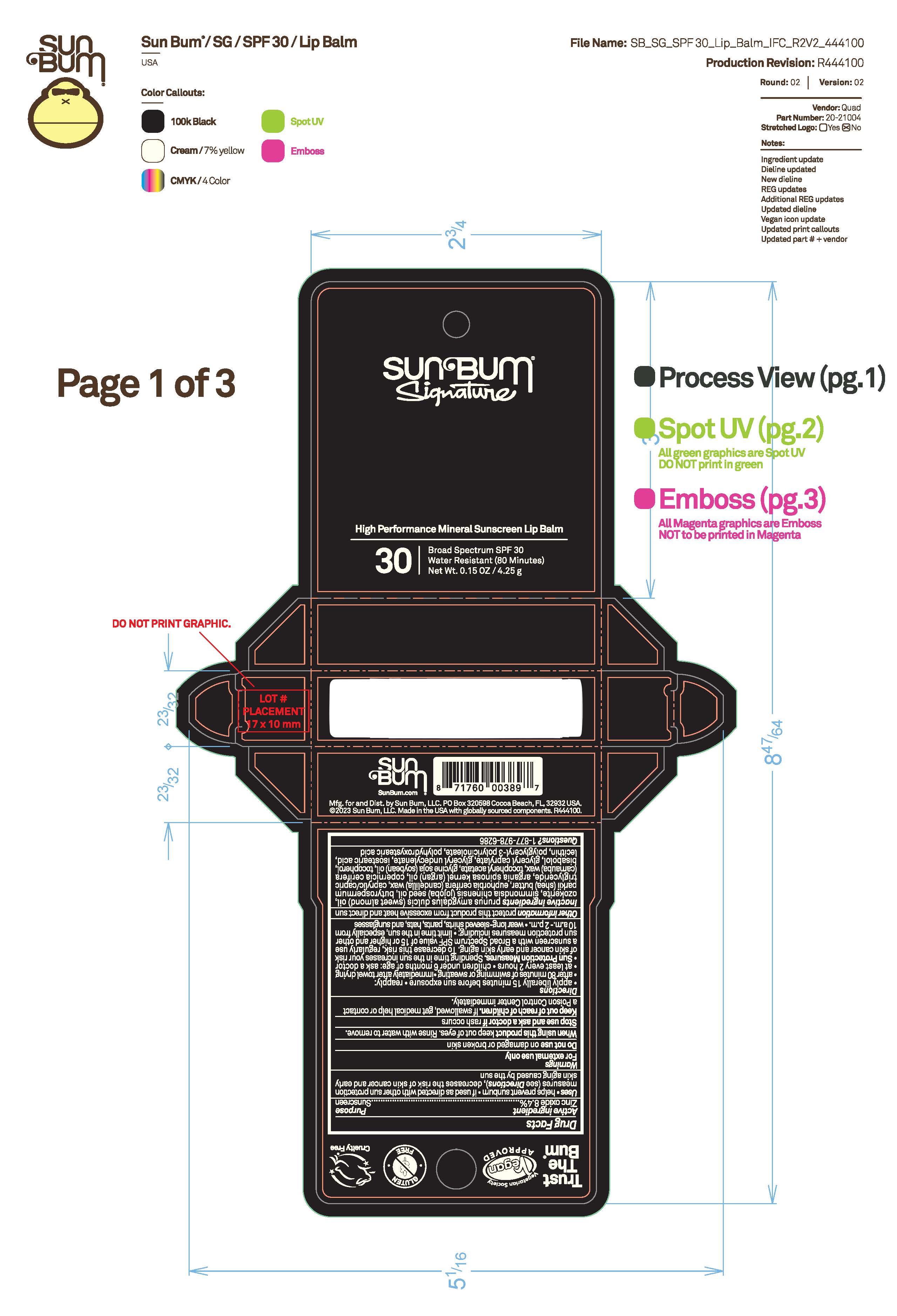 DRUG LABEL: Sun Bum Signature High Performance Mineral Sunscreen Lip Balm 30
NDC: 69039-812 | Form: STICK
Manufacturer: Sun Bum, LLC
Category: otc | Type: HUMAN OTC DRUG LABEL
Date: 20250819

ACTIVE INGREDIENTS: ZINC OXIDE 84 mg/1 g
INACTIVE INGREDIENTS: BISABOLOL; GLYCERYL CAPRYLATE; PRUNUS AMYGDALUS DULCIS (SWEET ALMOND) OIL; SIMMONDSIA CHINENSIS (JOJOBA) SEED OIL; BUTYROSPERMUM PARKII (SHEA) BUTTER; EUPHORBIA CERIFERA (CANDELILLA) WAX; TOCOPHEROL; GLYCERYL 1-UNDECYLENATE; LECITHIN, SUNFLOWER; CERESIN; POLYHYDROXYSTEARIC ACID (2300 MW); ISOSTEARIC ACID; POLYGLYCEROL POLYRICINOLEIC ACID; COPERNICIA CERIFERA (CARNAUBA) WAX; .ALPHA.-TOCOPHEROL ACETATE; ARGANIA SPINOSA KERNEL OIL; CAPRYLIC/CAPRIC TRIGLYCERIDE; SOYBEAN OIL

Sun Bum Signature High Performance Mineral Sunscreen Lip Balm 30

Active Ingredients

Zinc Oxide 8.4%

Purpose

Sunscreen

Uses

• helps prevent sunburn • if used as directed with other sun protection measures, (see Directions) decreases the risk of skin cancer and early skin aging caused by the sun

Warnings

For external use only

Do not use on damaged or broken skin

When using this product keep out of eyes. Rinse with water to remove.

Stop use and ask a doctor if rash occurs

Keep out of reach of children. If swallowed, get medical help or contact a Poison Control Center immediately.

Warnings

Keep Out Of Reach Of Children

Directions

• apply liberally 15 minutes before sun exposure

• reapply: • after 80 minutes of swimming or sweating • immediately after towel drying • at least every 2 hours

• children under 6 months of age: ask a doctor

• Sun Protection Measures. Spending time in the sun increases your risk of skin cancer and early skin aging. To decrease this risk, regularly use a sunscreen with a Broad Spectrum SPF value of 15 or higher and other sun protection measures including:

• limit time in the sun, especially from 10 a.m.- 2 p.m.

• wear long-sleeved shirts, pants, hats and sunglasses

Directions

• apply liberally 15 minutes before sun exposure

Other Information

protect this product from excessive heat and direct sun

Inactive Ingredients

prunus amygdalus dulcis (sweet almond) oil, ozokerite, simmondsia chinensis (jojoba) seed oil, butyrospermum parkii (shea) butter, euphorbia cerifera (candelilla) wax, caprylic/capric triglyceride, argania spinosa kernel (argan) oil, copernicia cerifera (carnauba) wax, tocopheryl acetate, glycine soja (soybean) oil, tocopherol, bisabolol, glyceryl caprylate, glyceryl undecylenate, isostearic acid, lecithin, polyglyceryl-3 polyricinoleate, polyhydroxystearic acid

Questions?

1-877-978-6286